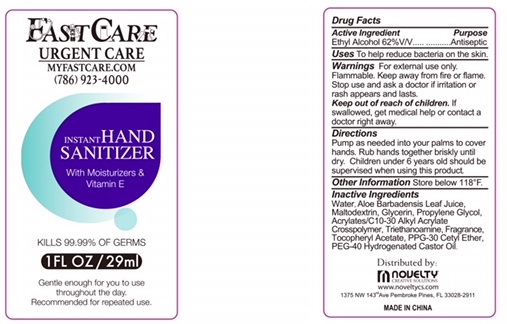 DRUG LABEL: Hand Sanitizer
NDC: 72180-001 | Form: GEL
Manufacturer: Novelty Creative Solutions, Inc.
Category: otc | Type: HUMAN OTC DRUG LABEL
Date: 20180324

ACTIVE INGREDIENTS: ALCOHOL 62 mL/100 mL
INACTIVE INGREDIENTS: POLYOXYL 40 HYDROGENATED CASTOR OIL; .ALPHA.-TOCOPHEROL ACETATE; ALOE VERA LEAF; PPG-30 CETYL ETHER; WATER; GLYCERIN; PROPYLENE GLYCOL; CARBOMER INTERPOLYMER TYPE A (55000 CPS); TROLAMINE; MALTODEXTRIN

Active Ingredient:
Ethyl Alcohol 62% V/V

Purpose

Antiseptic

Warnings

For external use only.

Flammable. Keep away from fire or flame.

Stop use and ask a doctor if irritation or rash appears and lasts.

Keep out of reach of children. If swallowed, get medical help or contact a doctor right away.

Directions

Pump as needed into your palms to cover hands. Rub hands together brisky unitl dry. Children under 6 years old should be supervised when using this product.

Inactive Ingredients

Water, Aloe Barbadensis Leaf Juice, Maltodextrin, Glycerin, Propylene Glycol, Acrylates/C10-30 Alkyl Acrylate, Crosspolymer, Triethanoamine, Fragrance, Tocopheryl Acetate, PPG-30 Cetyl Ether, PEG-40 Hydrogenated Castor Oil

Other Information Store below 118 F.

Uses

To help reduce bacteria on the skin.